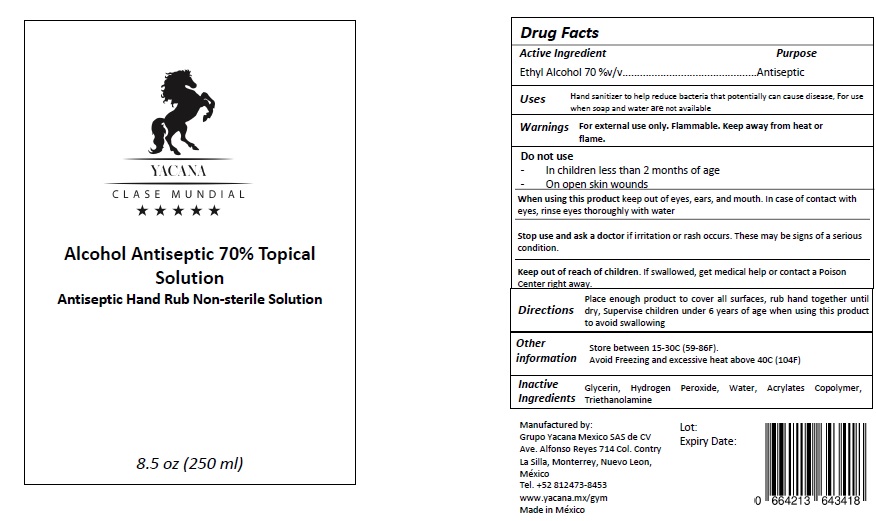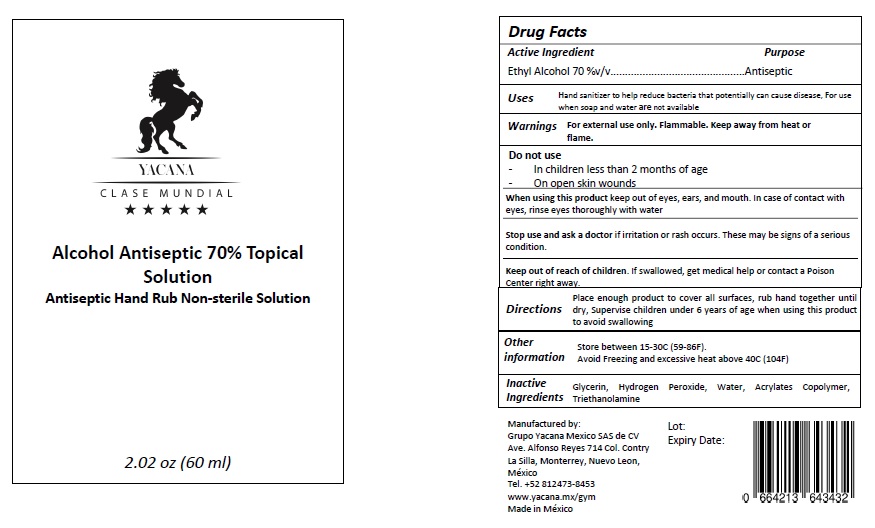 DRUG LABEL: Yacana
NDC: 76592-003 | Form: SOLUTION
Manufacturer: GRUPO YACANA MEXICO S.A.S. DE C.V.
Category: otc | Type: HUMAN OTC DRUG LABEL
Date: 20200515

ACTIVE INGREDIENTS: ALCOHOL 70 mL/100 mL
INACTIVE INGREDIENTS: DIMETHYLAMINOETHYL METHACRYLATE - BUTYL METHACRYLATE - METHYL METHACRYLATE COPOLYMER; WATER; HYDROGEN PEROXIDE; TROLAMINE; GLYCERIN

Alcohol Antiseptic 70% Topical Solution

Active lngredient

Ethyl Alcohol 70 %v/v...

Purpose

Antiseptic

Uses

Hand sanitizer to help reduce bacteria that potentially can cause disease, For use when soap and water are not available

Warnings

For external use only.

Flammable. Keep away from fire or flame.

Do not use

- In childrens less than 2 two months of age.
- on open wounds

When using this product keep out of eyes, ears, and mouth. In case of contact with eyes, rinse eyes thoroughly with water.

Stop use and ask a doctor if irritation or rash occurs. These may be signs of a serious condition.

Directions

Place enough product to cover all surfaces, rub hand together until dry, Supervise children under 6 years of age when using this product
to avoid swallowing.

Inactives

Glycerin, Hydrogen Peroxide, Water, Acrylates Copolymer,
Triethanolamine

Keep out of reach of children.

If swallowed, get medical help or contact a Poison Center right away.

Other information

- Store between 15-30C (59-86F).
- Avoid Freezing and excessive heat above 40C (104F)